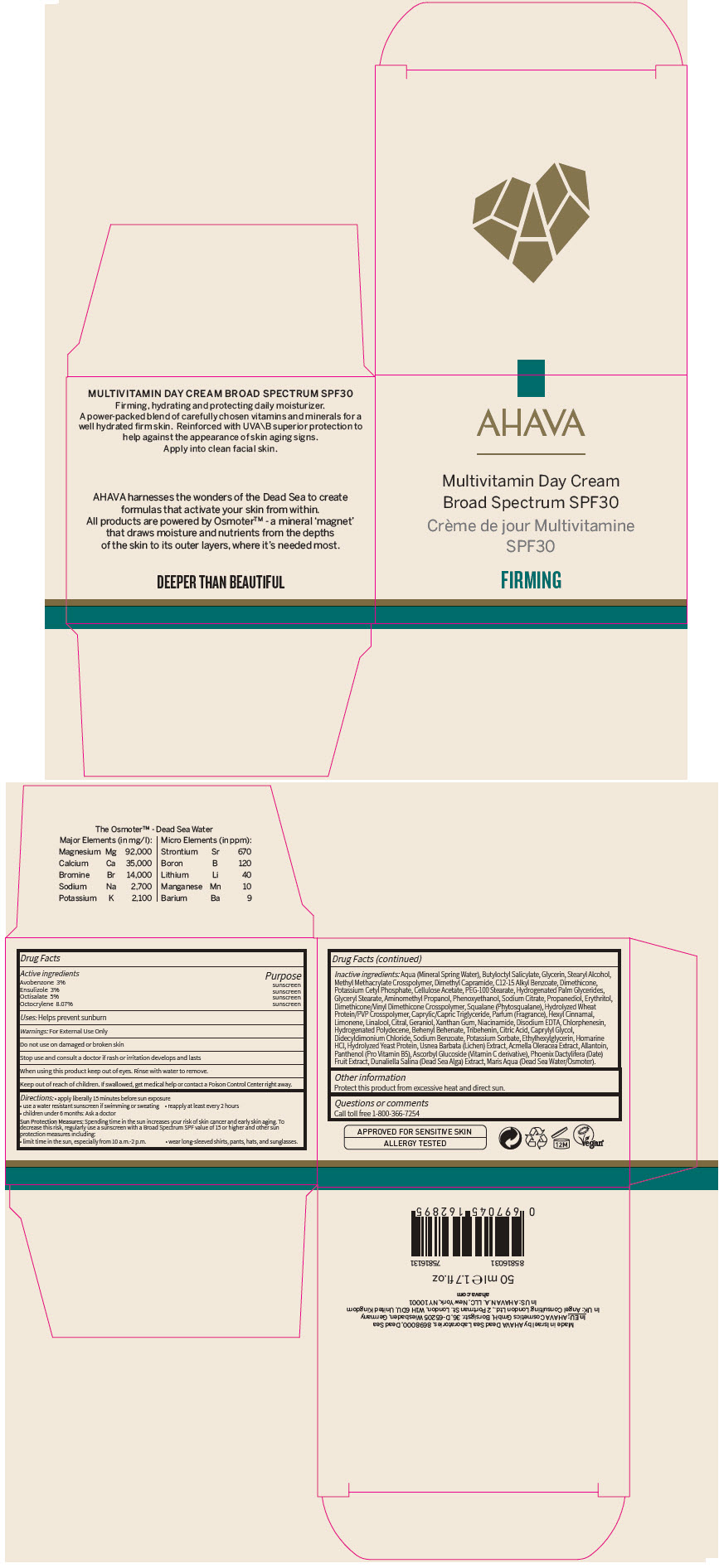 DRUG LABEL: AHAVA MultiVitamin Day SPF30
NDC: 60289-301 | Form: CREAM
Manufacturer: AHAVA - Dead Sea Laboratories Ltd
Category: otc | Type: HUMAN OTC DRUG LABEL
Date: 20241202

ACTIVE INGREDIENTS: Avobenzone 30 mg/1 mL; Ensulizole 30 mg/1 mL; Octisalate 50 mg/1 mL; Octocrylene 80.7 mg/1 mL
INACTIVE INGREDIENTS: WATER; BUTYLOCTYL SALICYLATE; GLYCERIN; STEARYL ALCOHOL; METHYL METHACRYLATE/GLYCOL DIMETHACRYLATE CROSSPOLYMER; DIMETHYL CAPRAMIDE; ALKYL (C12-15) BENZOATE; DIMETHICONE; POTASSIUM CETYL PHOSPHATE; CELLULOSE ACETATE; PEG-100 STEARATE; HYDROGENATED PALM GLYCERIDES; GLYCERYL MONOSTEARATE; AMINOMETHYLPROPANOL; PHENOXYETHANOL; SODIUM CITRATE, UNSPECIFIED FORM; PROPANEDIOL; ERYTHRITOL; MEDIUM-CHAIN TRIGLYCERIDES; .ALPHA.-HEXYLCINNAMALDEHYDE; LIMONENE, (+)-; LINALOOL, (+/-)-; CITRAL; GERANIOL; XANTHAN GUM; NIACINAMIDE; EDETATE DISODIUM ANHYDROUS; CHLORPHENESIN; BEHENYL BEHENATE; TRIBEHENIN; CITRIC ACID MONOHYDRATE; CAPRYLYL GLYCOL; DIDECYLDIMONIUM CHLORIDE; SODIUM BENZOATE; POTASSIUM SORBATE; ETHYLHEXYLGLYCERIN; HOMARINE HYDROCHLORIDE; USNEA BARBATA; ACMELLA OLERACEA FLOWERING TOP; ALLANTOIN; PANTHENOL; ASCORBYL GLUCOSIDE; DATE

AHAVA MultiVitamin Day Cream SPF30

Drug Facts

ACTIVE INGREDIENT

Active ingredients | Purpose
Avobenzone 3% | sunscreen
Ensulizole 3% | sunscreen
Octisalate 5% | sunscreen
Octocrylene 8.07% | sunscreen

Uses

Helps prevent sunburn

Warnings

For External Use Only

Do not use on damaged or broken skin

Stop use and consult a doctor if rash or irritation develops and lasts

When using this product keep out of eyes. Rinse with water to remove.

Keep out of reach of children. If swallowed, get medical help or contact a Poison Control Center right away.

Directions

- apply liberally 15 minutes before sun exposure
- use a water resistant sunscreen if swimming or sweating
- reapply at least every 2 hours
- children under 6 months: Ask a doctor

Sun Protection Measures: Spending time in the sun increases your risk of skin cancer and early skin aging. To decrease this risk, regularly use a sunscreen with a Broad Spectrum SPF value of 15 or higher and other sun protection measures including:

- limit time in the sun, especially from 10 a.m.-2 p.m.
- wear long-sleeved shirts, pants, hats, and sunglasses.

Inactive ingredients

Aqua (Mineral Spring Water), Butyloctyl Salicylate, Glycerin, Stearyl Alcohol, Methyl Methacrylate Crosspolymer, Dimethyl Capramide, C12-15 Alkyl Benzoate, Dimethicone, Potassium Cetyl Phosphate, Cellulose Acetate, PEG-100 Stearate, Hydrogenated Palm Glycerides, Glyceryl Stearate, Aminomethyl Propanol, Phenoxyethanol, Sodium Citrate, Propanediol, Erythritol, Dimethicone/Vinyl Dimethicone Crosspolymer, Squalane (Phytosqualane), Hydrolyzed Wheat Protein/PVP Crosspolymer, Caprylic/Capric Triglyceride, Parfum (Fragrance), Hexyl Cinnamal, Limonene, Linalool, Citral, Geraniol, Xanthan Gum, Niacinamide, Disodium EDTA, Chlorphenesin, Hydrogenated Polydecene, Behenyl Behenate, Tribehenin, Citric Acid, Caprylyl Glycol, Didecyldimonium Chloride, Sodium Benzoate, Potassium Sorbate, Ethylhexylglycerin, Homarine HCl, Hydrolyzed Yeast Protein, Usnea Barbata (Lichen) Extract, Acmella Oleracea Extract, Allantoin, Panthenol (Pro Vitamin B5), Ascorbyl Glucoside (Vitamin C derivative), Phoenix Dactylifera (Date) Fruit Extract, Dunaliella Salina (Dead Sea Alga) Extract, Maris Aqua (Dead Sea Water/Osmoter).

Other information

Protect this product from excessive heat and direct sun.

Questions or comments

Call toll free 1-800-366-7254

PRINCIPAL DISPLAY PANEL - 50 ml Jar Carton

AHAVA

Multivitamin Day Cream
Broad Spectrum SPF30

FIRMING